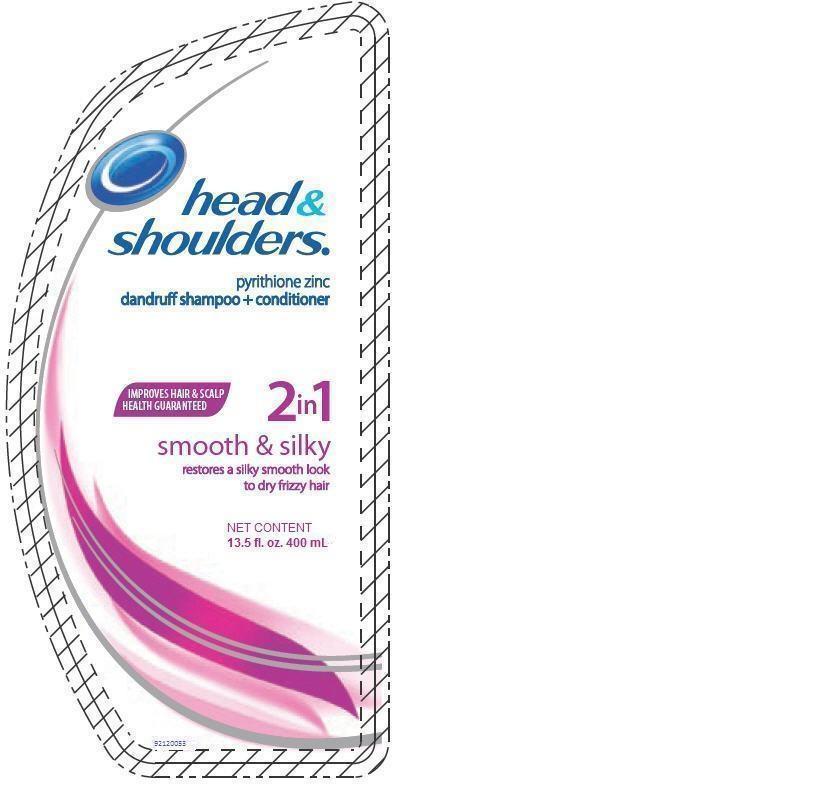 DRUG LABEL: Head and Shoulders
NDC: 51769-901 | Form: LOTION/SHAMPOO
Manufacturer: ALL NATURAL DYNAMICS
Category: otc | Type: HUMAN OTC DRUG LABEL
Date: 20131212

ACTIVE INGREDIENTS: Pyrithione Zinc 0.01 g/1 mL
INACTIVE INGREDIENTS: water; sodium lauryl sulfate; sodium laureth sulfate; glycol distearate; zinc carbonate; sodium chloride; dimethicone; COCO MONOETHANOLAMIDE; sodium benzoate; magnesium carbonate hydroxide; methylchloroisothiazolinone; methylisothiazolinone; POLYQUATERNIUM-10 (400 MPA.S AT 2%); Cetyl Alcohol; Magnesium Sulfate; ALOE VERA LEAF; Benzyl Alcohol; Sodium Xylenesulfonate

Head & Shoulders smooth and silky

Drug Facts

Active ingredient

Pyrithione zinc 1%

Purpose

Anti-dandruff

Uses

helps prevent recurrence of flaking and itching associated with dandruff.

Warnings

For external use only.

Directions

- for best results use at least twice a week or as directed by a doctor.
- for maximum dandruff control, use every time you shampoo.
- wet hair, massage onto scalp, rinse, repeat if desired.

When using this product

- avoid contact with eyes. If contact occurs, rinse eyes thoroughly with water.

Stop use and ask a doctor if

condition worsens or does not improve after regular use of this product as directed.

KEEP OUT OF REACH OF CHILDREN

Keep this and all drugs out of reach of children. If swallowed, get medical help or contact a Poison Control Center right away.

Inactive ingredients

Water, sodium lauryl sulfate, sodium laureth sulfate, glycol distearate, zinc carbonate, sodium chloride, fragrance, sodium xylenesulfonate, dimethicone, cocamidopropyl betaine, sodium benzoate, guar hydroxypropyltrimonium chloride, magnesium carbonate hydroxide, methylchloroisothiazolinone, methylisothiazolinone, pyrithione zinc, blue 1, red 33.

Questions (or comments)?

01-800-717-2413